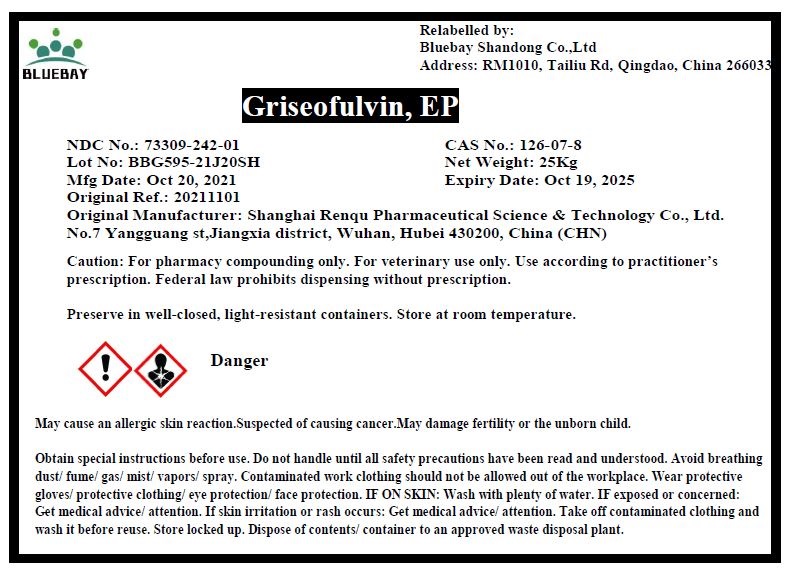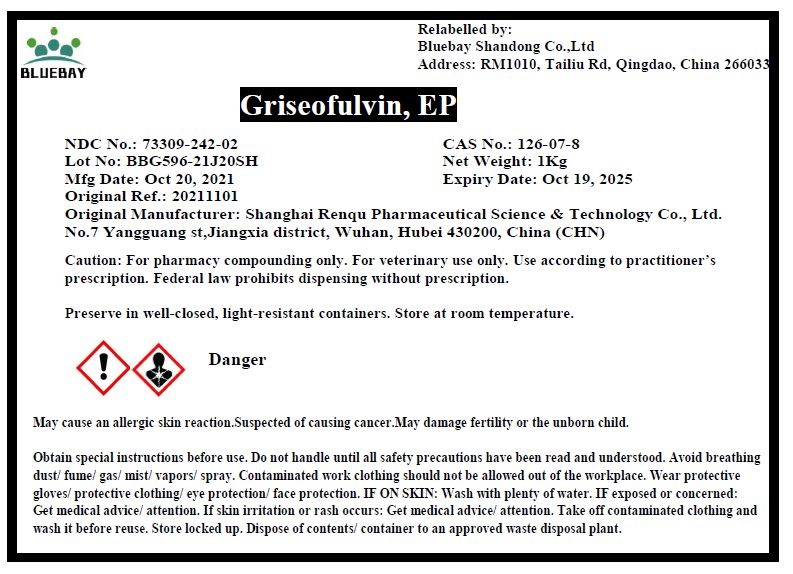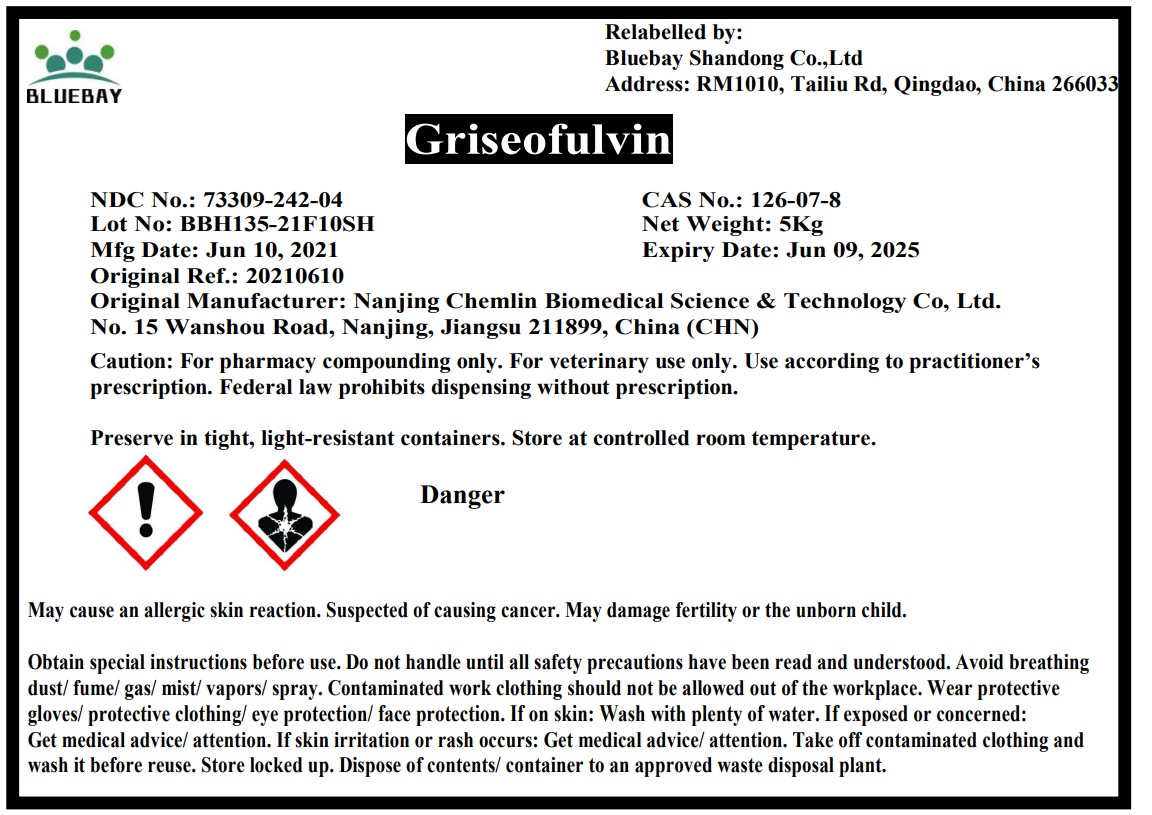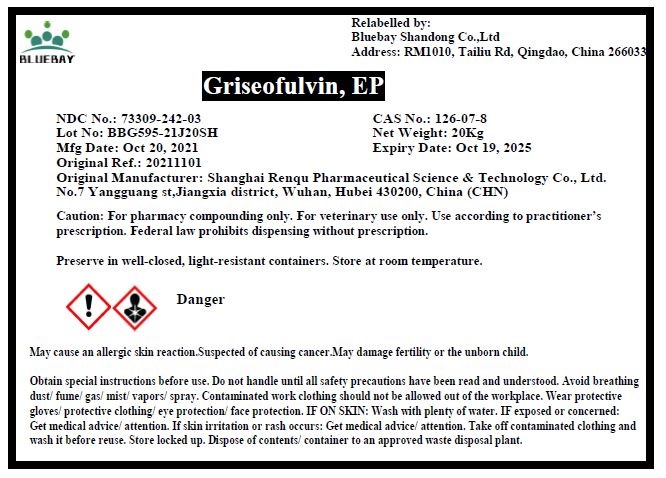 DRUG LABEL: Griseofulvin
NDC: 73309-242 | Form: POWDER
Manufacturer: BLUEBAY SHANDONG CO.,LTD
Category: other | Type: BULK INGREDIENT - ANIMAL DRUG
Date: 20220328

ACTIVE INGREDIENTS: Griseofulvin 1 kg/1 kg

Griseofulvin